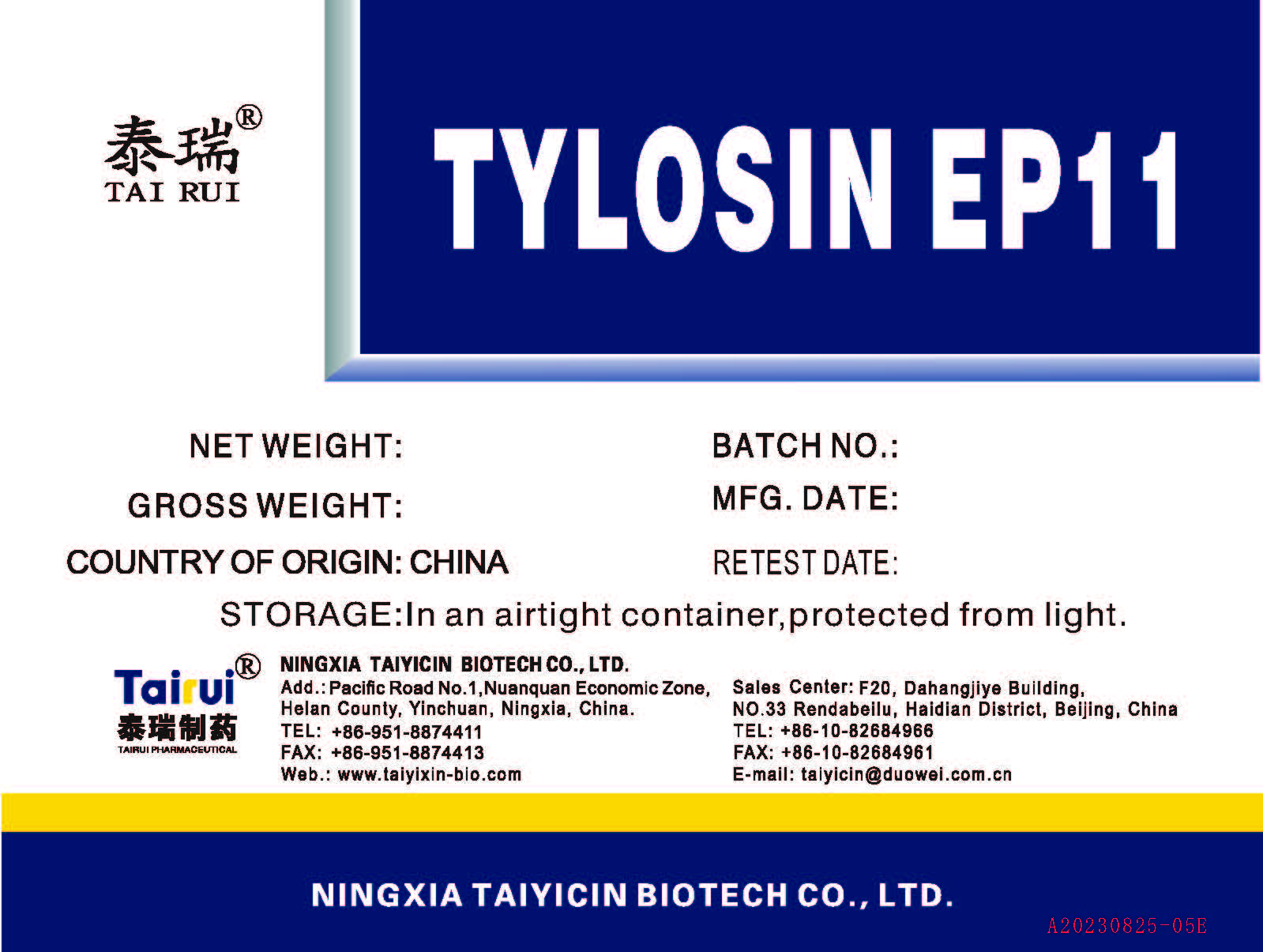 DRUG LABEL: Tylosin Base
NDC: 71949-0003 | Form: POWDER
Manufacturer: Ningxia Taiyicin Biotech Co., Ltd
Category: other | Type: BULK INGREDIENT - ANIMAL DRUG
Date: 20241217

ACTIVE INGREDIENTS: TYLOSIN 1 kg/1 kg

Tylosin Base